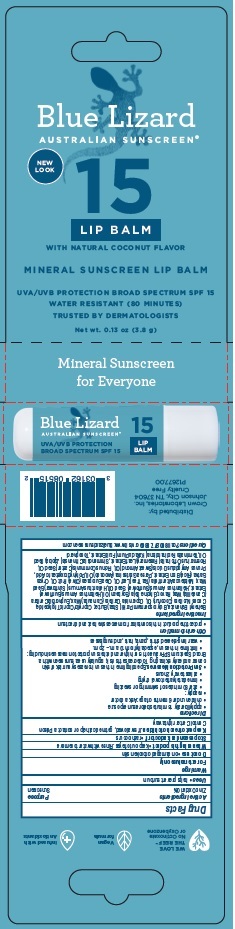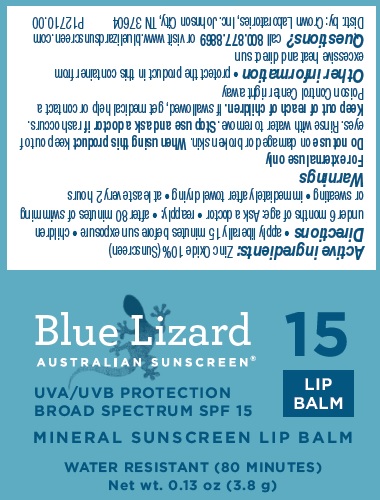 DRUG LABEL: Blue Lizard SPF 15 Lip Balm
NDC: 0316-2085 | Form: STICK
Manufacturer: Crown Laboratories
Category: otc | Type: HUMAN OTC DRUG LABEL
Date: 20260112

ACTIVE INGREDIENTS: ZINC OXIDE 10 mg/1 g
INACTIVE INGREDIENTS: CASTOR OIL; CARNAUBA WAX; .ALPHA.-TOCOPHEROL, D-; RICE BRAN; ALMOND OIL; HELIANTHUS ANNUUS SEED WAX; JOJOBA OIL; TEA TREE OIL; SOYBEAN OIL; ROSEMARY; HELIANTHUS ANNUUS FLOWERING TOP; BEHENYL BEHENATE; COCONUT OIL; POLYHYDROXYSTEARIC ACID STEARATE; MEDIUM-CHAIN TRIGLYCERIDES; SUNFLOWER OIL; CANDELILLA WAX; SHEA BUTTER; AVOCADO OIL; KAKADU PLUM; OLIVE OIL

Blue Lizard SPF 15 Lip Balm

Active ingredient

Zinc Oxide 10%

Purpose

Sunscreen

Uses

- helps prevent sunburn

Warnings

For external use only

Do not use

- on damaged or broken skin

When using this product

- keep out of eyes. Rinse with water to remove

Stop use and ask a doctor if

- rash occurs

Keep out of reach of children

- If swallowed, get medical help or contact a Poison Control Center right away.

Directions

• apply liberally 15 minutes before sun exposure

• children under 6 months of age: Ask a doctor

• reapply:

- after 80 minutes of swimming or sweating
- immediately after towel drying
- at least every 2 hours

• Sun Protection Measures. Spending time in the sun increases your risk of skin cancer and early skin aging. To decrease this risk, regularly use a sunscreen with a Broad Spectrum SPF value of 15 or higher and other sun protection measures including:

- limit time in the sun, especially from 10 a.m.- 2 p.m.
- wear long-sleeved shirts, pants, hats, and sunglasses

Other information

- Protect the product in this container from excessive heat and direct sun

Inactive ingredients

Behenyl Behenate, Butyrospermum Parkii (Shea) Butter, Caprylic/Capric Triglyceride, Cocos Nucifera (Coconut) Oil, Copernicia Cerifera (Carnauba) Wax, Euphorbia Cerifera (Candelilla) Wax, Flavor, Glycine Soja (Soybean) Oil, Helianthus Annuus (Sunflower) Extract, Helianthus Annuus (Sunflower) Seed Oil, Helianthus Annuus (Sunflower) Seed Wax, Melaleuca Alternifolia (Tea Tree) Leaf Oil, Olea Europaea (Olive) Fruit Oil, Oryza Sativa (Rice) Bran Extract, Persea Gratissima (Avocado) Oil, Polyhydroxystearic Acid, Prunus Amygdalus Dulcis (Sweet Almond) Oil, Ricinus Communis (Castor) Seed Oil, Rosmarinus Officinalis (Rosemary) Leaf Extract, Simmondsia Chinensis (Jojoba) Seed Oil, Terminalia Ferdinandiana (Kakadu Plum) Fruit Extract, Tocopherol

Questions?

Call 800.877.8869 or visit www.bluelizardsunscreen.com

Blue Lizard SPF 15 Lip Balm Label

BLUE LIZARD

AUSTRALIAN SUNSCREEN

15

LIP BALM

UVA/UVB PROTECTION

BROAD SPECTRUM SPF 15

MINERAL SUNSCREEN LIP BALM

WATER RESISTANT (80 Minutes)

Net wt. 0.13 oz (3.8 g)